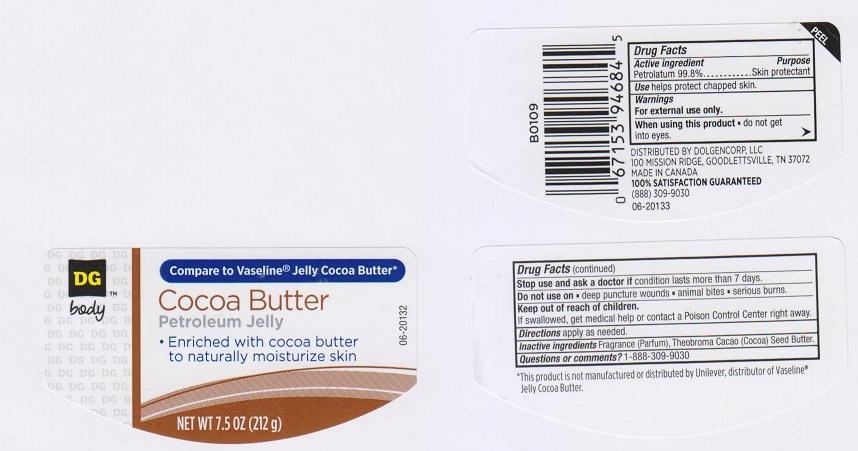 DRUG LABEL: DG BODY
NDC: 55910-317 | Form: JELLY
Manufacturer: DOLGENCORP INC
Category: otc | Type: HUMAN OTC DRUG LABEL
Date: 20150227

ACTIVE INGREDIENTS: PETROLATUM 99.8 g/100 g
INACTIVE INGREDIENTS: COCOA BUTTER

DRUG FACTS

ACTIVE INGREDIENT

PETROLATUM 99.8%

PURPOSE

SKIN PROTECTANT

USE

HELPS PROTECT CHAPPED SKIN

WARNINGS

FOR EXTERNAL USE ONLY

WHEN USING THIS PRODUCT

DO NOT GET INTO EYES

STOP USE AND ASK A DOCTOR IF

CONDITION LASTS MORE THAN 7 DAYS

DO NOT USE ON

- DEEP PUNCTURE WOUNDS
- ANIMAL BITES
- SERIOUS BURNS

KEEP OUT OF REACH OF CHILDREN

IF SWALLOWED, GET MEDICAL HELP OR CONTACT A POISON CONTROL CENTER RIGHT AWAY

DIRECTIONS

APPLY AS NEEDED

INACTIVE INGREDIENTS

FRAGRANCE (PARFUM), THEOBROMA CACAO (COCOA) SEED BUTTER

QUESTIONS OR COMMENTS?

1-888-309-9030